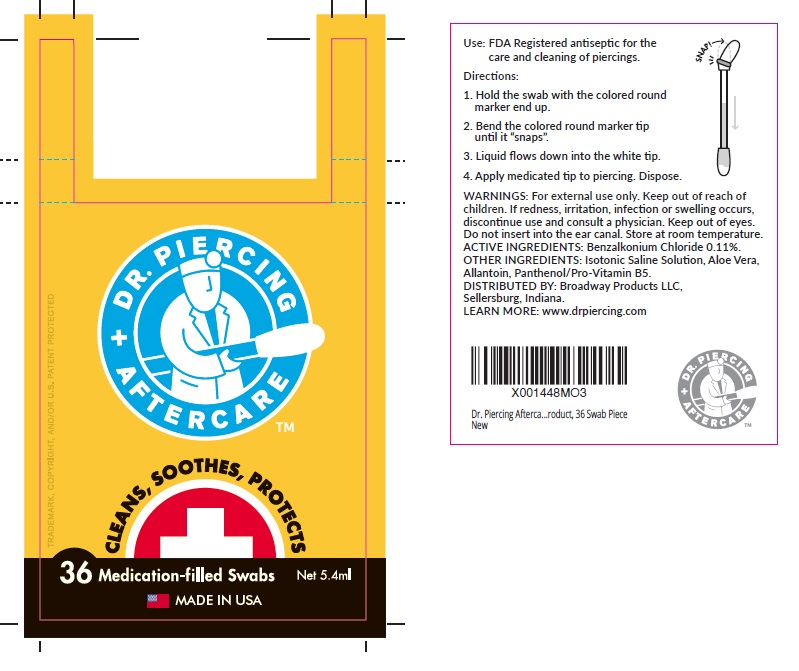 DRUG LABEL: Dr. Piercing Aftercare
NDC: 65734-504 | Form: SWAB
Manufacturer: Swabplus, L.P.
Category: otc | Type: HUMAN OTC DRUG LABEL
Date: 20230110

ACTIVE INGREDIENTS: BENZALKONIUM CHLORIDE 1.1 mg/1 mL
INACTIVE INGREDIENTS: ALOE VERA LEAF; METHYLCHLOROISOTHIAZOLINONE; MAGNESIUM CHLORIDE; PANTHENOL; METHYLISOTHIAZOLINONE; MAGNESIUM NITRATE; CUPRIC NITRATE; WATER; COCAMIDOPROPYL BETAINE; TROLAMINE; SODIUM CHLORIDE; ALLANTOIN

Dr. Piercing Aftercare 36CT

Use

Use: FDA Registered antiseptic for the care and cleaning of piercings.

Directions:

1. Hold swab with the colored round marker end up.

2. Bend the colored round marker tip until it "snaps".

3. Liquid flows down into the white tip.

4. Apply medicated tip to piercing. Dispose.

WARNINGS:

WARNINGS: For external use only. If redness, irritation, infection or swelling occurs, discontinue use and consult a physician. Keep out of eyes. Do not insert into the ear canal. Store at room temprature.

KEEP OUT OF REACH OF CHILDREN

ACTIVE INGREDIENTS

ACTIVE INGREDIENTS: Benzalkonium Chloride 0.11%

OTHER INGREDIENTS

OTHER INGREDIENTS: Isotonic Saline Solution, Aloe Vera, Allantoin, Panthenol/Pro-Vitamin B5.

DISTRIBUTED BY

DISTRIBUTED BY: Broadway Products LLC, Sellersburg, Indiana.

LEARN MORE: www.drpiercing.com

BARCODE XM001448MO3

Dr. Piercing Afterca...roduct, 36 Swab Pierce New

Principal Display Label

DR. PIERCING AFTERCARE™

CLEAN, SOOTHES, PROTECTS

36 Medication-filled Swabs Net 5.4mL

MADE IN USA